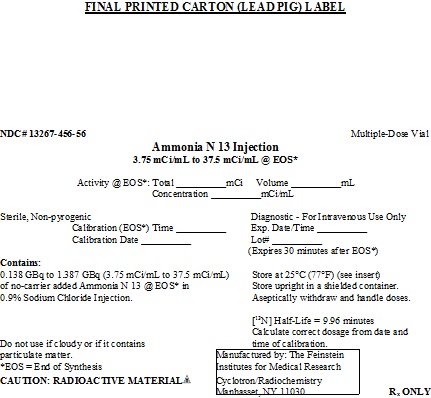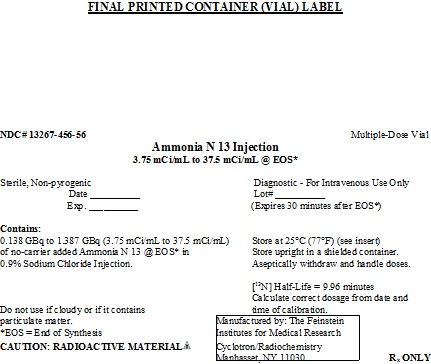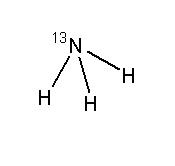 DRUG LABEL: Ammonia N 13
NDC: 13267-456 | Form: INJECTION
Manufacturer: THE FEINSTEIN INSTITUTES FOR MEDICAL RESEARCH
Category: prescription | Type: HUMAN PRESCRIPTION DRUG LABEL
Date: 20191030

ACTIVE INGREDIENTS: AMMONIA N-13 37.5 mCi/1 mL

HIGHLIGHTS OF PRESCRIBING INFORMATION

These highlights do not include all the information needed to use Ammonia N 13 Injection safely and effectively. See full prescribing information for Ammonia N 13 Injection.
Ammonia N 13 Injection for intravenous use
Initial U.S. Approval: 2007

1 INDICATIONS AND USAGE

Ammonia N 13 Injection is a radioactive diagnostic agent for Positron Emission Tomography (PET) indicated for diagnostic PET imaging of the myocardium under rest or pharmacologic stress conditions to evaluate myocardial perfusion in patients with suspected or existing coronary artery disease.

2 DOSAGE AND ADMINISTRATION

Rest Imaging Study (2.1):
• Aseptically withdraw Ammonia N 13 Injection from its container and administer 10-20 mCi (0.370 – 0.740 GBq) as a bolus through a catheter inserted into a large peripheral vein.
• Start imaging 3 minutes after the injection and acquire images for a total of 10-20 minutes.

Stress Imaging Study (2.2):
• If a rest imaging study is performed, begin the stress imaging study 40 minutes or more after the first Ammonia N 13 Injection to allow sufficient isotope decay.
• Administer a pharmacologic stress-inducing drug in accordance with its labeling.
• Aseptically withdraw Ammonia N 13 Injection from its container and administer 10-20 mCi (0.370 – 0.740 GBq) of Ammonia N 13 Injection as a bolus at 8 minutes after the administration of the pharmacologic stress-inducing drug.
• Start imaging 3 minutes after the Ammonia N 13 Injection and acquire images for a total of 10-20 minutes.

Patient Preparation (2.3):
• To increase renal clearance of radioactivity and to minimize radiation dose to the bladder, hydrate the patient before the procedure and encourage voiding as soon as each image acquisition is completed and as often as possible thereafter for at least one hour.

3 DOSAGE FORMS AND STRENGTHS

Glass vial containing 0.138-1.387 GBq (3.75-37.5 mCi/mL) of Ammonia N 13 Injection in aqueous 0.9 % sodium chloride solution (approximately 8 mL volume).

4 CONTRAINDICATIONS

None

5 WARNINGS AND PRECAUTIONS

Ammonia N 13 Injection may increase the risk of cancer. Use the smallest dose necessary for imaging and ensure safe handling to protect the patient and health care worker.

6 ADVERSE REACTIONS

No adverse reactions have been reported for Ammonia N 13 Injection based on a review of the published literature, publicly available reference sources, and adverse drug reaction reporting system.

To report SUSPECTED ADVERSE REACTIONS, contact The Feinstein Institutes for Medical Research at 516-562-1052 or FDA at 1-800-FDA-1088 or www.fda.gov/medwatch.

8 USE IN SPECIFIC POPULATIONS

• It is not known whether this drug is excreted in human milk. Alternatives to breastfeeding (e.g. using stored breast milk or infant formula) should be used for 2 hours (>10 half-lives of radioactive decay for N 13 isotope) after administration of Ammonia N 13 Injection (8.3).
• The safety and effectiveness of Ammonia N 13 Injection has been established in pediatric patients (8.4).

FULL PRESCRIBING INFORMATION

1 INDICATIONS AND USAGE

Ammonia N 13 Injection is indicated for diagnostic Positron Emission Tomography (PET) imaging of the myocardium under rest or pharmacologic stress conditions to evaluate myocardial perfusion in patients with suspected or existing coronary artery disease.

2 DOSAGE AND ADMINISTRATION

2.1 Rest Imaging Study

• Aseptically withdraw Ammonia N 13 Injection from its container and administer 10-20 mCi (0.370 – 0.740 GBq) as a bolus through a catheter inserted into a large peripheral vein.

• Start imaging 3 minutes after the injection and acquire images for a total of 10-20 minutes.

2.2 Stress Imaging Study

• If a rest imaging study is performed, begin the stress imaging study 40 minutes or more after the first Ammonia N 13 Injection to allow sufficient isotope decay.

• Administer a pharmacologic stress-inducing drug in accordance with its labeling.

• Aseptically withdraw Ammonia N 13 Injection from its container and administer 10-20 mCi (0.370 – 0.740 GBq) of Ammonia N 13 Injection as a bolus at 8 minutes after the administration of the pharmacologic stress-inducing drug.

• Start imaging 3 minutes after the Ammonia N 13 Injection and acquire images for a total of 10-20 minutes.

2.3 Patient Preparation

To increase renal clearance of radioactivity and to minimize radiation dose to the bladder, ensure that the patient is well hydrated before the procedure and encourage voiding as soon as a study is completed and as often as possible thereafter for at least one hour.

2.4 Radiation Dosimetry

The converted radiation absorbed doses in rem/mCi are shown in Table 1. These estimates are calculated from the Task Group of Committee 2 of the International Commission on Radiation Protection.^1

Table 1. N 13 Absorbed Radiation Dose Per Unit Activity (rem/mCi) for Adults and Pediatric Groups
Organ | Adult | 15 - year old | 10 - year old | 5 - year old | 1 - year old
Adrenals | 0.0085 | 0.0096 | 0.016 | 0.025 | 0.048
Bladder wall | 0.030 | 0.037 | 0.056 | 0.089 | 0.17
Bone surfaces | 0.0059 | 0.0070 | 0.011 | 0.019 | 0.037
Brain | 0.016 | 0.016 | 0.017 | 0.019 | 0.027
Breast | 0.0067 | 0.0067 | 0.010 | 0.017 | 0.033
Stomach wall | 0.0063 | 0.0078 | 0.012 | 0.019 | 0.037
Small intestine | 0.0067 | 0.0081 | 0.013 | 0.021 | 0.041
*ULI | 0.0067 | 0.0078 | 0.013 | 0.021 | 0.037
**LLI | 0.0070 | 0.0078 | 0.013 | 0.020 | 0.037
Heart | 0.0078 | 0.0096 | 0.015 | 0.023 | 0.041
Kidneys | 0.017 | 0.021 | 0.031 | 0.048 | 0.089
Liver | 0.015 | 0.018 | 0.029 | 0.044 | 0.085
Lungs | 0.0093 | 0.011 | 0.018 | 0.029 | 0.056
Ovaries | 0.0063 | 0.0085 | 0.014 | 0.021 | 0.041
Pancreas | 0.0070 | 0.0085 | 0.014 | 0.021 | 0.041
Red marrow | 0.0063 | 0.0078 | 0.012 | 0.020 | 0.037
Spleen | 0.0093 | 0.011 | 0.019 | 0.030 | 0.056
Testes | 0.0067 | 0.0070 | 0.011 | 0.018 | 0.035
Thyroid | 0.0063 | 0.0081 | 0.013 | 0.021 | 0.041
Uterus | 0.0070 | 0.0089 | 0.014 | 0.023 | 0.041
Other tissues | 0.0059 | 0.0070 | 0.011 | 0.018 | 0.035

*Upper large intestine, **Lower large intestine

2.5 Drug Handling

• Inspect Ammonia N 13 Injection visually for particulate matter and discoloration before administration, whenever solution and container permit.

• Do not administer Ammonia N 13 Injection containing particulate matter or discoloration; dispose of these unacceptable or unused preparations in a safe manner, in compliance with applicable regulations.

• Wear waterproof gloves and effective shielding when handling Ammonia N 13 Injection.

• Use aseptic technique to maintain sterility during all operations involved in the manipulation and administration of Ammonia N 13 Injection. The contents of each vial are sterile and non-pyrogenic.

• Use appropriate safety measures, including shielding, consistent with proper patient management to avoid unnecessary radiation exposure to the patient, occupational workers, clinical personnel, and other persons.

• Radiopharmaceuticals should be used by or under the control of physicians who are qualified by specific training and experience in the safe use and handling of radionuclides, and whose experience and training have been approved by the appropriate governmental agency authorized to license the use of radionuclides.

• Before administration of Ammonia N 13 Injection, assay the dose in a properly calibrated dose calibrator.

3 DOSAGE FORMS AND STRENGTHS

Glass vial (25 mL) containing 0.138-1.387 GBq (3.75-37.5 mCi/mL) of Ammonia N 13 Injection in aqueous 0.9 % sodium chloride solution (approximately 8 mL volume) that is suitable for intravenous administration.

4 CONTRAINDICATIONS

None

5 WARNINGS AND PRECAUTIONS

5.1 Radiation Risks

Ammonia N 13 Injection may increase the risk of cancer. Use the smallest dose necessary for imaging and ensure safe handling to protect the patient and health care worker [see Dosage and Administration (2.4)].

6 ADVERSE REACTIONS

No adverse reactions have been reported for Ammonia N 13 Injection based on a review of the published literature, publicly available reference sources, and adverse drug reaction reporting systems. However, the completeness of these sources is not known.

7 DRUG INTERACTIONS

The possibility of interactions of Ammonia N 13 Injection with other drugs taken by patients undergoing PET imaging has not been studied.

8 USE IN SPECIFIC POPULATIONS

8.1 Pregnancy

Pregnancy Category C
Animal reproduction studies have not been conducted with Ammonia N 13 Injection. It is also not known whether Ammonia N 13 Injection can cause fetal harm when administered to a pregnant woman or can affect reproduction capacity. Ammonia N 13 Injection should be given to a pregnant woman only if clearly needed.

8.3 Nursing Mothers

It is not known whether this drug is excreted in human milk. Because many drugs are excreted in human milk and because of the potential for radiation exposure to nursing infants from Ammonia N 13 Injection, use alternative infant nutrition sources (e.g. stored breast milk or infant formula) for 2 hours (>10 half-lives of radioactive decay for N 13 isotope) after administration of the drug or avoid use of the drug, taking into account the importance of the drug to the mother.

8.4 Pediatric Use

The safety and effectiveness of Ammonia N 13 Injection has been established in pediatric patients based on known metabolism of ammonia, radiation dosimetry in the pediatric population, and clinical studies in adults [see Dosage and Administration (2.4)].

11 DESCRIPTION

11.1 Chemical Characteristics

Ammonia N 13 Injection is a positron emitting radiopharmaceutical that is used for diagnostic purposes in conjunction with positron emission tomography (PET) imaging. The active ingredient, [^13N] ammonia, has the molecular formula of ^13NH3 with a molecular weight of 16.02, and has the following chemical structure:

Ammonia N 13 Injection is provided as a ready to use sterile, pyrogen-free, clear, and colorless solution. Each mL of the solution contains between 0.138 GBq to 1.387 GBq (3.75 mCi to 37.5 mCi) of [^13N] ammonia, at the end of synthesis (EOS) reference time, in 0.9% aqueous sodium chloride. The pH of the solution is between 4.5 to 7.5. The recommended dose of radioactivity (10-20 mCi) is associated with a theoretical mass dose of 0.05-0.1 picomoles (8.47-16.94 picograms) of ammonia.

11.2 Physical Characteristics

Nitrogen N 13 decays by emitting positron to Carbon C 13 (stable) and has a physical half-life of 9.96 minutes. The principal photons useful for imaging are the dual 511 keV gamma photons that are produced and emitted simultaneously in opposite direction when the positron interacts with an electron (Table 2).

Table 2. Principal Radiation Emission Data for Nitrogen 13
Radiation/Emission | % Per Disintegration | Energy
Positron(β+) | 100 | 1190 keV (Max.)
Gamma(±)* | 200 | 511 keV

*Produced by positron annihilation

The specific gamma ray constant (point source air kerma coefficient) for nitrogen N 13 is 5.9 R/hr/mCi (1.39 x 10^-6 Gy/hr/kBq) at 1 cm. The half-value layer (HVL) of lead (Pb) for 511 keV photons is 4 mm. Selected coefficients of attenuation are listed in Table 3 as a function of lead shield thickness. For example, the use of 39 mm thickness of lead will attenuate the external radiation by a factor of about 1000.

Table 3. Radiation Attenuation of 511 keV Photons by lead (Pb) shielding
Shield Thickness (Pb) mm | Coefficient of Attenuation
4 | 0.5
8 | 0.25
13 | 0.1
26 | 0.01
39 | 0.001
52 | 0.0001

Table 4 lists fractions remaining at selected time intervals from the calibration time. This information may be used to correct for physical decay of the radionuclide.

Table 4. Physical Decay Chart for Nitrogen N 13
Minutes | Fraction Remaining
0* | 1.000
5 | 0.706
10 | 0.499
15 | 0.352
20 | 0.249
25 | 0.176
30 | 0.124

*Calibration time

12 CLINICAL PHARMACOLOGY

12.1 Mechanism of Action

Ammonia N 13 Injection is a radiolabeled analog of ammonia that is distributed to all organs of the body after intravenous administration. It is extracted from the blood in the coronary capillaries into the myocardial cells where it is metabolized to glutamine N 13 and retained in the cells. The presence of ammonia N 13 and glutamine N 13 in the myocardium allows for PET imaging of the myocardium.

12.2 Pharmacodynamics

Following intravenous injection, ammonia N 13 enters the myocardium through the coronary arteries. The PET technique measures myocardial blood flow based on the assumption of a three-compartmental disposition of intravenous ammonia N 13 in the myocardium. In this model, the value of the rate constant, which represents the delivery of blood to myocardium, and the fraction of ammonia N 13 extracted into the myocardial cells, is a measure of myocardial blood flow. Optimal PET imaging of the myocardium is generally achieved between 10 to 20 minutes after administration.

12.3 Pharmacokinetics

Following intravenous injection, Ammonia N 13 Injection is cleared from the blood with a biologic half-life of about 2.84 minutes (effective half-life of about 2.21 minutes). In the myocardium, its biologic half-life has been estimated to be less than 2 minutes (effective half-life less than 1.67 minutes).

The mass dose of Ammonia N 13 Injection is very small as compared to the normal range of ammonia in the blood (0.72-3.30 mg) in a healthy adult man [see Description (11.1)].

Plasma protein binding of ammonia N 13 or its N 13 metabolites has not been studied.

Ammonia N 13 undergoes a five-enzyme step metabolism in the liver to yield urea N 13 (the main circulating metabolite). It is also metabolized to glutamine N 13 (the main metabolite in tissues) by glutamine synthesis in the skeletal muscles, liver, brain, myocardium, and other organs. Other metabolites of ammonia N 13 include small amounts of N 13 amino acid anions (acidic amino acids) in the forms of glutamate N 13 or aspartate N 13.

Ammonia N 13 is eliminated from the body by urinary excretion mainly as urea N 13.

The pharmacokinetics of Ammonia N 13 Injection have not been studied in renally impaired, hepatically impaired, or pediatric patients.

13 NONCLINICAL TOXICOLOGY

13.1 Carcinogenesis, Mutagenesis, Impairment of Fertility

Long term animal studies have not been performed to evaluate the carcinogenic potential of Ammonia N 13 Injection. Genotoxicity assays and impairment of male and female fertility studies with Ammonia N 13 Injection have not been performed.

14 CLINICAL STUDIES

In a descriptive, prospective, blinded image interpretation study^2 of adult patients with known or suspected coronary artery disease, myocardial perfusion deficits in stress and rest PET images obtained with Ammonia N 13 (N=111) or Rubidium 82 (N=82) were compared to changes in stenosis flow reserve (SFR) as determined by coronary angiography. The principal outcome of the study was the evaluation of PET defect severity relative to SFR.

PET perfusion defects at rest and stress for seven cardiac regions (anterior, apical, anteroseptal, posteroseptal, anterolateral, posterolateral, and inferior walls) were graded on a 0 to 5 scale defined as normal (0), possible (1), probable (2), mild (3), moderate (4), and severe (5) defects. Coronary angiograms were used to measure absolute and relative stenosis dimensions and to calculate stenosis flow reserve defined as the maximum value of flow at maximum coronary vasodilatation relative to rest flow under standardized hemodynamic conditions. SFR scores ranged from 0 (total occlusion) to 5 (normal).

With increasing impairment of flow reserve, the subjective PET defect severity increased. A PET defect score of 2 or higher was positively correlated with flow reserve impairment (SFR<3).

15 REFERENCES

^1Annals of the ICRP. Publication 53. Radiation dose to patients from radiopharmaceuticals. New York: Pergamon Press, 1988.
^2Demer, L.L.K.L. Gould, R.A. Goldstein, R.L. Kirkeeide, N.A. Mullani, R.W. Smalling, A. Nishikawa, and M.E. Merhige. Assessment of coronary artery disease severity by PET: Comparison with quantitative arteriography in 193 patients. Circulation 1989; 79: 825-35.

16 HOW SUPPLIED/STORAGE AND HANDLING

Ammonia N 13 Injection is packaged in 25 mL multiple dose glass vial containing between 1.11 GBq to 11.1 GBq (30 mCi to 300 mCi) of [^13N] ammonia, at the end of synthesis (EOS) reference time, in 0.9% sodium chloride injection solution in approximately 8 mL volume. The recommended dose of radioactivity (10-20 mCi) is associated with a theoretical mass dose of 0.05-0.1 picomoles (8.47-16.94 picograms) of Ammonia.

Storage
Store at 25°C (77°F); excursions permitted to 15-30°C (59-86°F). Use the solution within 30 minutes of the End of Synthesis (EOS) calibration.

17 PATIENT COUNSELING INFORMATION

17.1 Pre-study Hydration

Instruct patients to drink plenty of water or other fluids (as tolerated) in the 4 hours before their PET study.

17.2 Post-study Voiding

Instruct patients to void after completion of each image acquisition session and as often as possible for one hour after the PET scan ends.

17.3 Post-study Breastfeeding Avoidance

Instruct nursing patients to substitute stored breast milk or infant formula for breast milk for 2 hours after administration of Ammonia N 13 Injection.

Manufactured & Distributed by:
The Feinstein Institutes for Medical Research
Cyclotron/Radiochemistry Facility
350 Community Drive
Manhasset, New York 11030